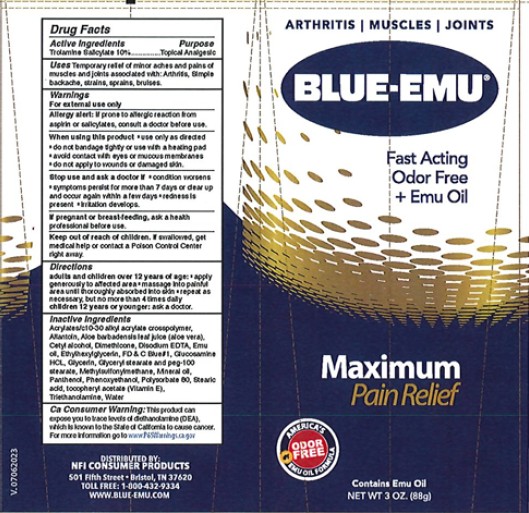 DRUG LABEL: Blue-Emu Maximum Pain Relief
NDC: 69993-300 | Form: CREAM
Manufacturer: Kingsway Pharmaceuticals dba NFI, LLC
Category: otc | Type: HUMAN OTC DRUG LABEL
Date: 20250909

ACTIVE INGREDIENTS: TROLAMINE SALICYLATE 0.1 g/1 g
INACTIVE INGREDIENTS: CARBOMER INTERPOLYMER TYPE A (ALLYL SUCROSE CROSSLINKED); ALLANTOIN; ALOE VERA LEAF; CETYL ALCOHOL; DIMETHICONE, UNSPECIFIED; EDETATE DISODIUM ANHYDROUS; EMU OIL; ETHYLHEXYLGLYCERIN; FD&C BLUE NO. 1; GLUCOSAMINE HYDROCHLORIDE; GLYCERIN; GLYCERYL STEARATE/PEG-100 STEARATE; DIMETHYL SULFONE; MINERAL OIL; PANTHENOL; PHENOXYETHANOL; POLYSORBATE 80; STEARIC ACID; TROLAMINE; .ALPHA.-TOCOPHEROL; WATER

Blue-Emu® Maximum Pain Relief Cream

Active Ingredients

Trolamine Salicylate 10%

Purpose

Topical Analgesic

Uses

Temporarily relief of minor aches and pains of muscles and joints associated with:

- Arthritis
- Simple backache
- strains
- sprains
- bruises

Warnings

For external use only

Allergy alert:

If prone to allergic reaction from aspirin or salicylates, consult a doctor before use.

When using this product

- use only as directed
- do not bandage tightly or use with a heating pad
- avoid contact with eyes or mucous membranes
- do not apply to wounds or damaged skin.

Stop use and ask a doctor if

- condition worsens
- symptoms persist for more than 7 days or clear up and occur again within a few days
- redness is present
- irritation develops.

PREGNANCY OR BREAST FEEDING

If pregnant or breast-feeding, ask a health professional before use.

Keep out of reach of children. If swallowed, get medical help or contact a Poison Control Center right away.

Directions

adults and children over 12 years of age:

- apply generously to affected area
- massage into painful area until thoroughly absorbed into skin
- repeat as necessary, but no more than 4 times daily

children 12 years or younger: ask a doctor.

Inactive Ingredients

acrylates/c10-30 alkyl acrylate crosspolymer, allantoin, aloe barbadensis leaf juice (aloe vera), cetyl alcohol, dimethicone, disodium EDTA, emu oil, ethylhexylglycerin, FD & C Blue#1, glucosamine HCl, glycerin, glyceryl stearate and peg-100 stearate, methylsulfonylmethane, mineral oil, panthenol, phenoxyethanol, polysorbate 80, stearic acid, tocopheryl acetate (Vitamin E), triethanolamine, water.

DISTRIBUTED BY:
NFI CONSUMER PRODUCTS
501 Fifth Street • Bristol, TN 37620
TOLL FREE: 1-800-432-9334
WWW.BLUE-EMU.COM

Ca Consumer Warning:

This product can expose you to trace levels of diethanolamine (DEA), which is know to the State of California to cause cancer. For more information go to www.P65Warnings.ca.gov

PRINCIPAL DISPLAY PANEL - 88 g Tube Label

ARTHRITIS | MUSCLES | JOINTS

BLUE-EMU®

Fast Acting
Odor Free
+ Emu Oil

Maximum
Pain Relief

AMERICA'S
#1
EMU OIL FORMULA
ODOR
FREE

Contains Emu Oil
NET WT 3 OZ. (88g)